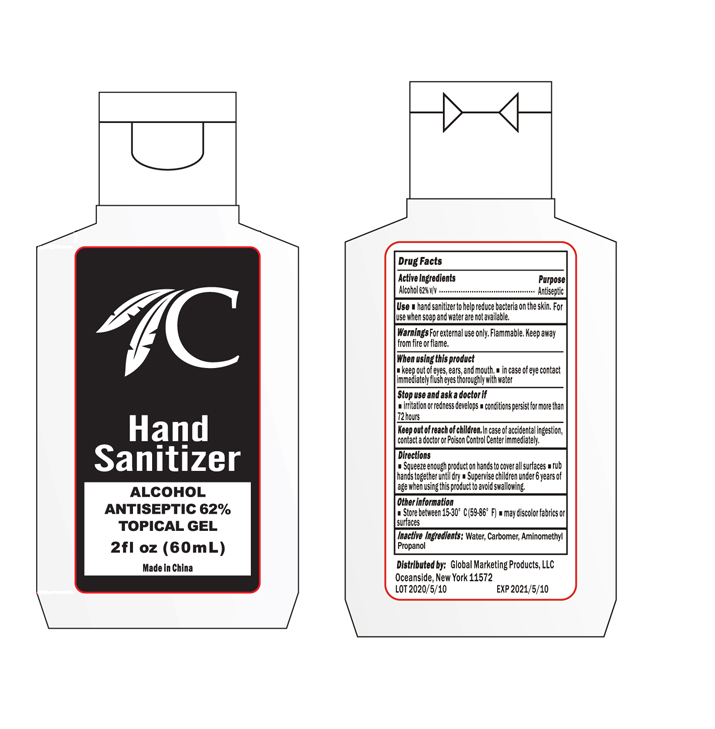 DRUG LABEL: Hand Sanitizer
NDC: 76750-002 | Form: GEL
Manufacturer: Global Marketing Products LLC
Category: otc | Type: HUMAN OTC DRUG LABEL
Date: 20200513

ACTIVE INGREDIENTS: ALCOHOL 62 mL/100 mL
INACTIVE INGREDIENTS: CARBOMER HOMOPOLYMER, UNSPECIFIED TYPE; AMINOMETHYLPROPANOL; WATER

Global Marketing II Hand Sanitizer

Active Ingredients

Alcohol 62% v/v

Purpose

Antiseptic

Use

■ hand sanitizer to help reduce bacteriaon the skin. For use when soap and water are not available.

Warnings

For external use only. Flammable. Keep away from heat or flame

When using this product

■ keep out of eyes, ears, and mouth. ■ in case of eye contact immediately flush eyes thoroughly with water.

Stop use and ask a doctor if

■ irritation or redness develops ■ conditions persist for more than 72 hours

Keep out of reach of children

In case of accidental ingestion, contact a doctor or Poison Control Center immediately.

Directions

■ Squeeze enough product on hands to cover all surfaces ■ rub hands together until dry ■ Supervise children under 6 years of age when using this product to avoid swallowing

Other information

■ Store between 15-30 C (59-86F) ■ may discolor fabrics or surfaces

Inactive ingredients

Water, Carbomer, Aminomethyl Propanol